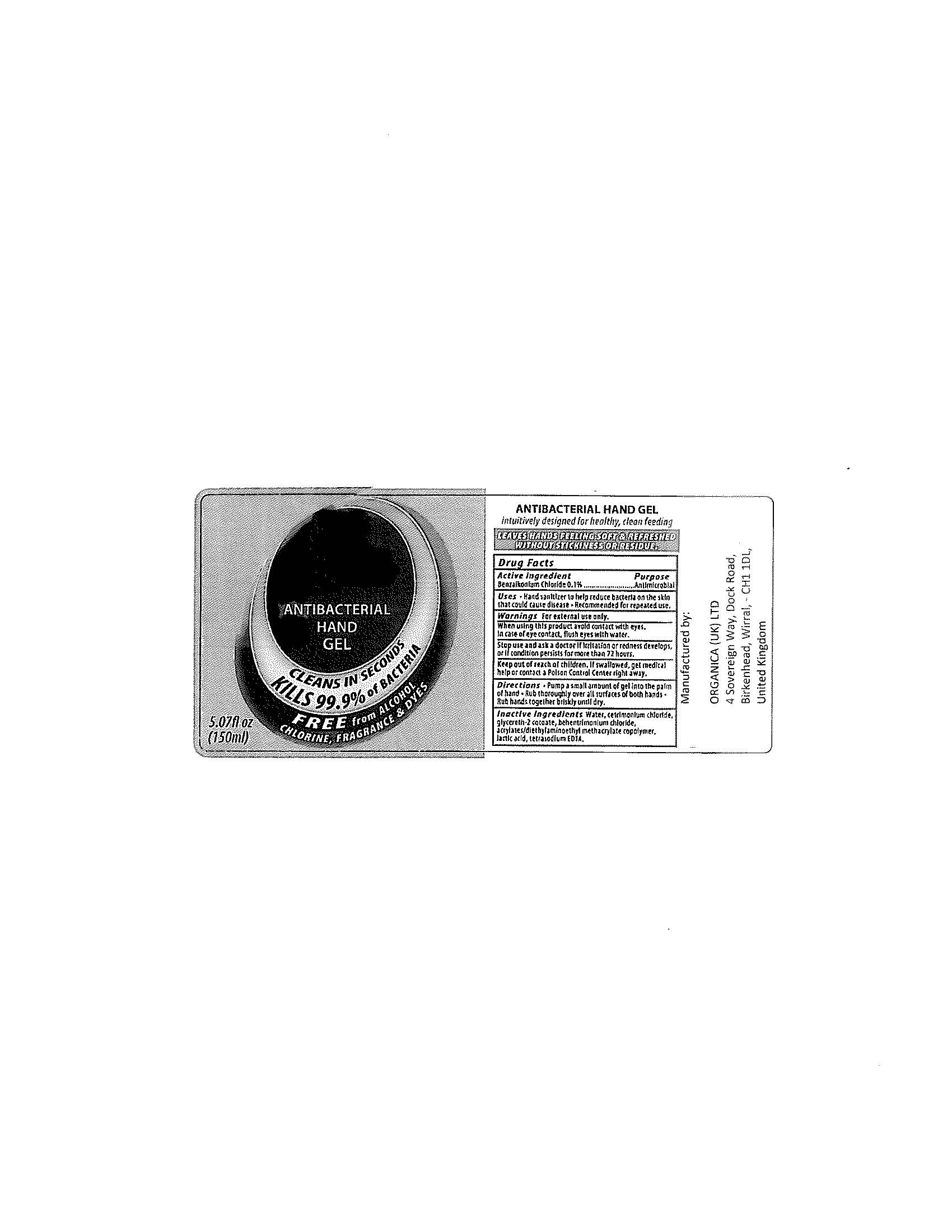 DRUG LABEL: Antibacterial Hand
NDC: 76268-001 | Form: GEL
Manufacturer: ORGANICA (UK) LTD
Category: otc | Type: HUMAN OTC DRUG LABEL
Date: 20111213

ACTIVE INGREDIENTS: BENZALKONIUM CHLORIDE  0.1 mL/100 mL
INACTIVE INGREDIENTS: WATER; CETRIMONIUM CHLORIDE; GLYCERETH-2 COCOATE; BEHENTRIMONIUM CHLORIDE; LACTIC ACID; EDETATE SODIUM

Drug Facts

Active ingredient

Benzalkonium Chloride 0.1%

Purpose

Antimicrobial

Uses

Hand sanitizer to help reduce bacteria on the skin that could cause disease

Recommended for repeated use.

Warnings

For external use only.

When using this product avoid contact with eyes.

In case of eye contact, flush eyes with water.

Stop use and ask a doctor if irritation or redness develops, or if condition persists for more than 72 hours.

Keep out of reach of children.

If swallowed, get medical help or contact a Poison Control Center right away.

Directions

Pump a small amount of gel into the palm of hand

Rub thoroughly over all surfaces of both hands

Rub hands together until dry.

Inactive ingredients

Water, cetrimonium chloride, glycereth-2 cocoate, behentrimonium chloride, acrylates/diethylaminoethyl methacrylate copolymer, lactic acid, tetrasodium EDTA.

PACKAGE LABEL

ANTIBACTERIAL HAND GEL

CLEANS IN SECONDS

KILLS 99.9% of BACTERIA

FREE from ALCOHOL

CHLORINE, FRAGRANCE and DYES

5.07fl 0z

(150ml)